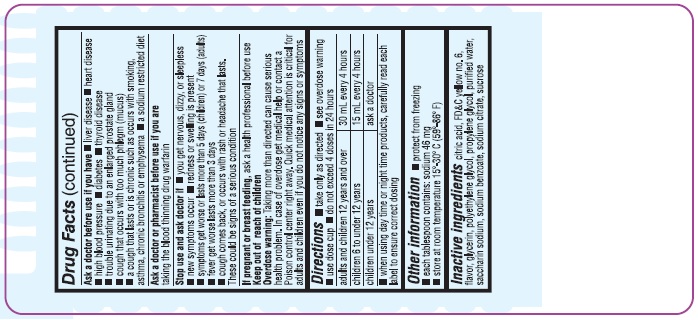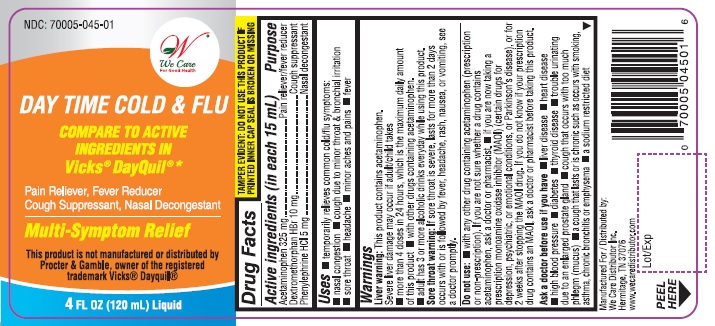 DRUG LABEL: Day Time Cold and Flu
NDC: 70005-045 | Form: SOLUTION
Manufacturer: We Care Distributor Inc.
Category: otc | Type: HUMAN OTC DRUG LABEL
Date: 20160805

ACTIVE INGREDIENTS: ACETAMINOPHEN 325 mg/15 mL; DEXTROMETHORPHAN HYDROBROMIDE 10 mg/15 mL; PHENYLEPHRINE HYDROCHLORIDE 5 mg/15 mL
INACTIVE INGREDIENTS: CITRIC ACID ACETATE; FD&C YELLOW NO. 6; GLYCERIN; POLYETHYLENE GLYCOLS; PROPYLENE GLYCOL; WATER; SACCHARIN SODIUM; SUCROSE; SODIUM BENZOATE; SODIUM CITRATE

DayTime Cold and Flu Drug Facts

Active ingredients (in each 15 mL)

Acetaminophen 325 mg

Dextromethorphan HBr 10 mg

Phenylephrine HCl 5 mg

Purpose

Pain reliever/fever reducer

Cough suppressant

Nasal decongestant

Uses

temporarily relieves common cold/flu symptoms:

- nasal congestion
- cough due to minor throat and bronchial irritation
- sore throat
- headache
- minor aches and pains
- fever

Warnings

Liver warning: This product contains acetaminophen. Severe liver damage may occur if adult/child takes

• more than 4 doses in 24 hours, which is the maximum daily amount for this product

• with other drugs containing acetaminophen

• adult has 3 or more alcoholic drinks every day while using this product

Sore throat warning: If sore throat is severe, lasts for more than 2 days, occurs with or followed by fever, headache, rash, nausea, or vomiting, see a doctor promptly.

Do not use

• with any other drug containing acetaminophen (prescription or nonprescription). If you are not sure whether a drug contains acetaminophen, ask a doctor or pharmacist.• if you are now taking a prescription monoamine oxidase inhibitor (MAOI) (certain drugs for depression, psychiatric, or emotional conditions, or Parkinson’s disease), or for 2 weeks after stopping the MAOI drug. If you do not know if your prescription drug contains an MAOI, ask a doctor or pharmacist before taking this product.

Ask a doctor before use if you have

- liver disease
- heart disease
- high blood pressure
- diabetes
- thyroid disease
- trouble urinating due to an enlarged prostate gland
- cough that occurs with too much phlegm (mucus)
- persistent or chronic cough as occurs with smoking, asthma, or emphysema
- a sodium restricted diet

Ask a doctor or pharmacist before use if you are

taking the blood thinning drug warfarin

Stop use and ask a doctor if

- you get nervous, dizzy or sleepless
- new symptoms occur
- redness or swelling is present
- symptom gets worse or lasts more than 5 days (children) or 7 days (adults)
- fever gets worse or lasts more than 3 days
- cough comes back or occurs with rash or headache that lasts.

These could be signs of a serious condition.

If pregnant or breast-feeding,

ask a health professional before use.

Keep out of reach of children.

Overdose warning: Taking more than directed cause serious health problems. In case of overdose, get medical help or contact a Poison Control Center right away. Quick medical attention is critical for adults as well as for children even if you do not notice any signs or symptoms.

Directions

- take only as directed – see Overdose warning
- use dose cup
- do not exceed 4 doses per 24 hrs
- adults & children 12 years and over: 30 mL every 4 hrs
- children 6 to under 12 years: 15 mL every 4 hrs
- children under 12 years: ask a doctor

When using Day Time and Night Time products; carefully read each label to ensure correct dosing

Other information

- protect from freezing
- each tablespoon contains: sodium 46 mg
- store at room temperature 15-30°C (59-86°F)

Inactive ingredients

citric acid, FD&C yellow no. 6, flavor, glycerin, polyethylene glycol, propylene glycol, purified water, saccharin sodium, sodium benzoate, sodium citrate, sucrose

Questions or comments?

1-888-705-WECARE (Mon-Fri 9am-5pm EST) or www.wecaredistributor.com

Principal Display Panel

SEE NEW WARNINGS

Compare to DayQuil® Cold & Flu Active Ingredients

Non-Drowsy

DayTime Cold & Flu

Pain Reliever, Fever Reducer, Cough Suppressant, Nasal Decongestant Multi-Symptom Relief

Aches, fever - Acetaminophen

Cough - Dextromethorphan HBr

Nasal congestion - Phenylephrine HCl

Alcohol Free and Antihistamine Free

4 FL OZ (120 mL)